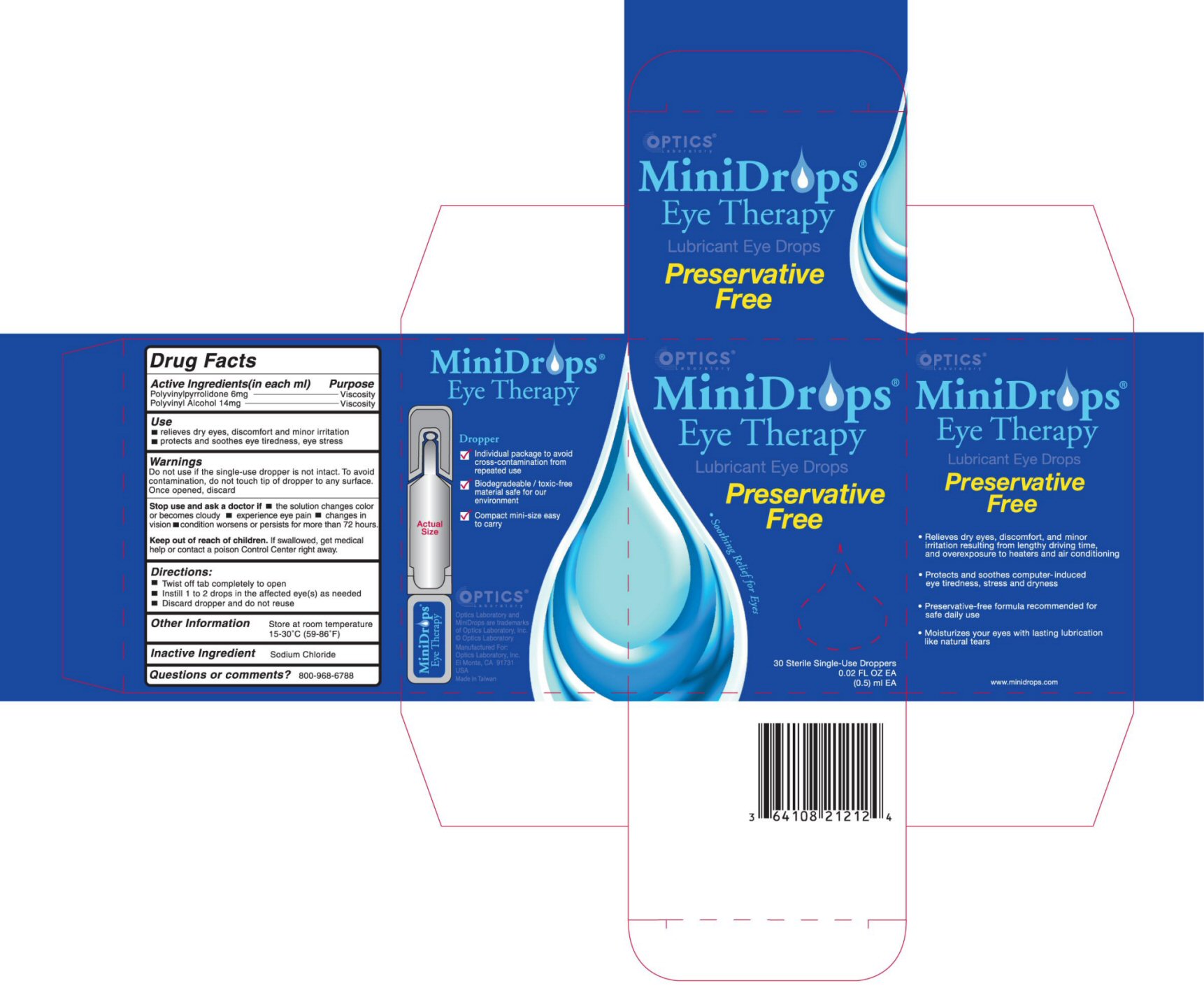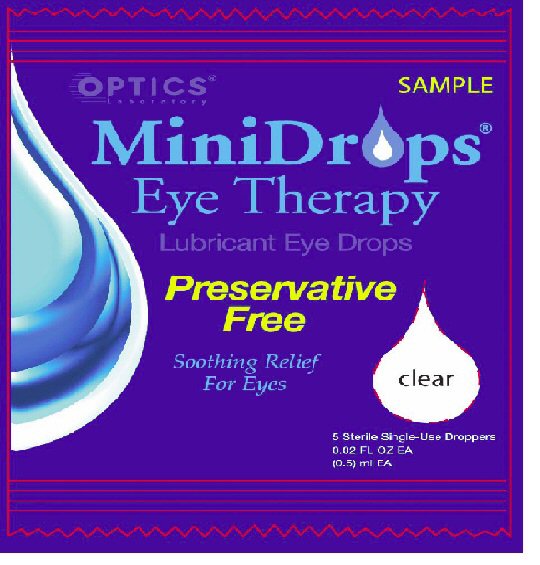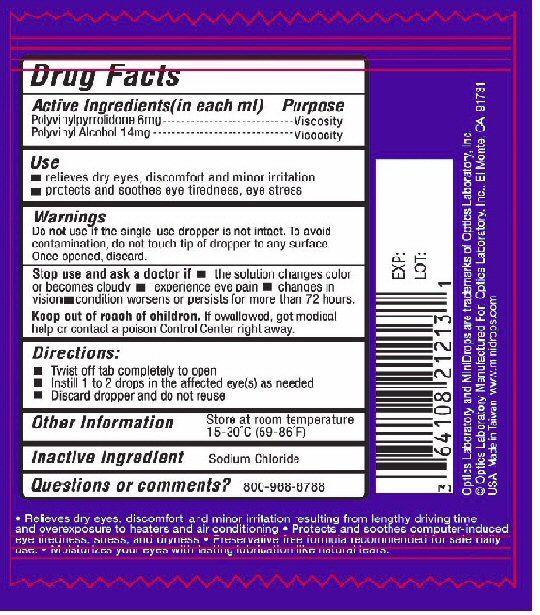 DRUG LABEL: MiniDrops
NDC: 62622-124 | Form: LIQUID
Manufacturer: Taiwan Biotech Co, Ltd
Category: otc | Type: HUMAN OTC DRUG LABEL
Date: 20100101

ACTIVE INGREDIENTS: POVIDONE K30 .6 mL/100 mL; POLYVINYL ALCOHOL 1.4 mL/100 mL
INACTIVE INGREDIENTS: SODIUM CHLORIDE .9 mL/100 mL; WATER 97.1 mL/100 mL

ACTIVE INGREDIENTS (in each ml)

Polyvinylpyrrolidone 6 mg

Polyvinyl Alcohol 14mg

PURPOSE

PURPOSE VISCOSITY

PURPOSE VISCOSITY

USE

RELIEVES DRY EYES, DISCOMFORT AND MINOR IRRITATION
PROTECTS AND SOOTHES EYE TIREDNESS, EYE STRESS

WARNINGS

DO NOT USE IF THE SINGLE-USE DROPPER IS NOT INTACT. TO AVOID CONTAMINATION, DO NOT TOUCH TIP OF DROPPER TO ANY SURFACE. ONCE OPENED, DISCARD.

STOP USE AND ASK A DOCTOR IF

- THE SOLUTION CHANGES COLOR OR BECOMES CLOUDY
- EXPERIENCE EYE PAIN
- CHANGES IN VISION
- CONDITION WORSENS OR PERSISTS FOR MORE THAN 72 HOURS.

KEEP OUT OF REACH OF CHILDREN

IF SWALLOWED GET MEDICAL HELP OR CONTACT A POISON CONTROL CENTER RIGHT AWAY.

DIRECTIONS

- TWIST OFF TAB COMPLETELY TO OPEN
- INSTILL 1 TO 2 DROPS IN THE AFFECTED EYE(S) AS NEEDED
- DISCARD DROPPER AND DO NOT REUSE

OTHER INFORMATION

STORE AT ROOM TEMPERATURE 15-30^0 C (59-86^0 F)

INACTIVE INGREDIENT

SODIUM CHLORIDE

QUESTIONS OR COMMENTS?

800-968-6788